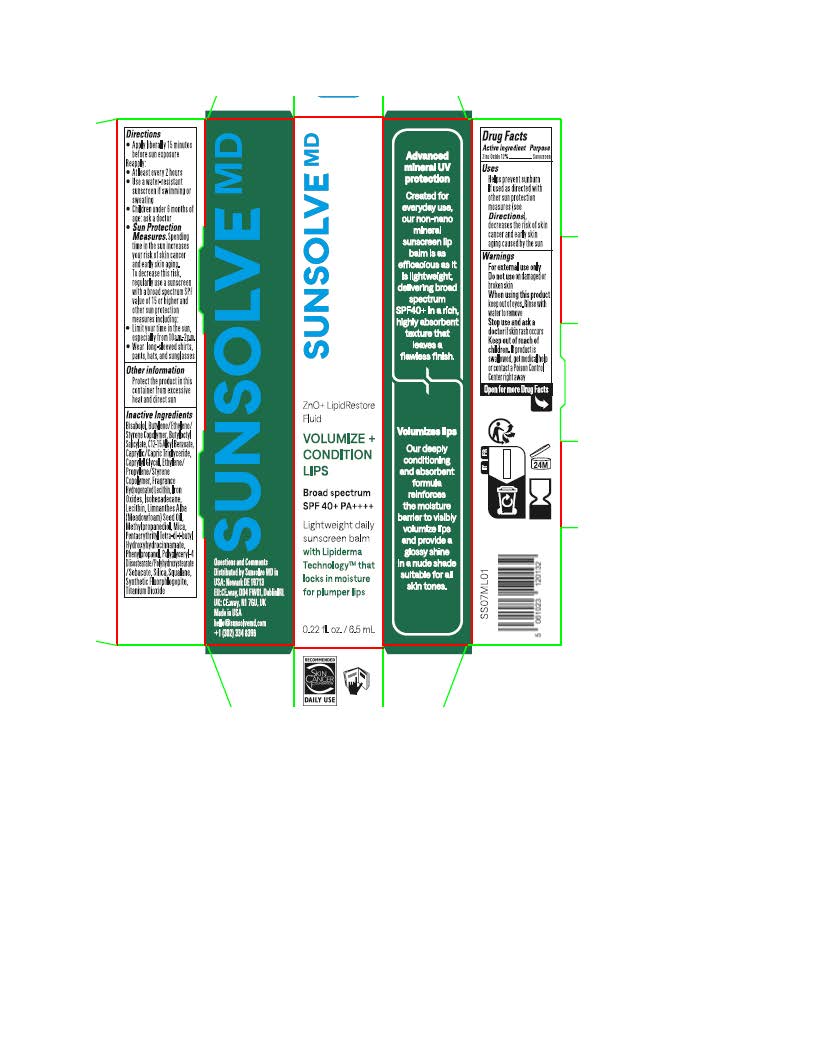 DRUG LABEL: Sunsolve MD Volumize and Condition Lip
NDC: 84878-107 | Form: LOTION
Manufacturer: Sunsolve MD
Category: otc | Type: HUMAN OTC DRUG LABEL
Date: 20251114

ACTIVE INGREDIENTS: ZINC OXIDE 132 mg/1 mL
INACTIVE INGREDIENTS: PENTAERYTHRITYL TETRA-DI-T-BUTYL HYDROXYHYDROCINNAMATE; ISOHEXADECANE; .ALPHA.-BISABOLOL, (+)-; FERRIC OXIDE RED; ALKYL (C12-15) BENZOATE; CAPRYLIC/CAPRIC TRIGLYCERIDE; CAPRYLYL GLYCOL; POLYGLYCERYL-4 DIISOSTEARATE/POLYHYDROXYSTEARATE/SEBACATE; LIMNANTHES ALBA (MEADOWFOAM) SEED OIL; SILICON DIOXIDE; MICA; TITANIUM DIOXIDE; FERRIC OXIDE YELLOW; FERROSOFERRIC OXIDE; METHYLPROPANEDIOL; LECITHIN, SOYBEAN; SQUALANE; BUTYLOCTYL SALICYLATE; PHENYLPROPANOL

Sunsolve MD Volumize and Condition Lip